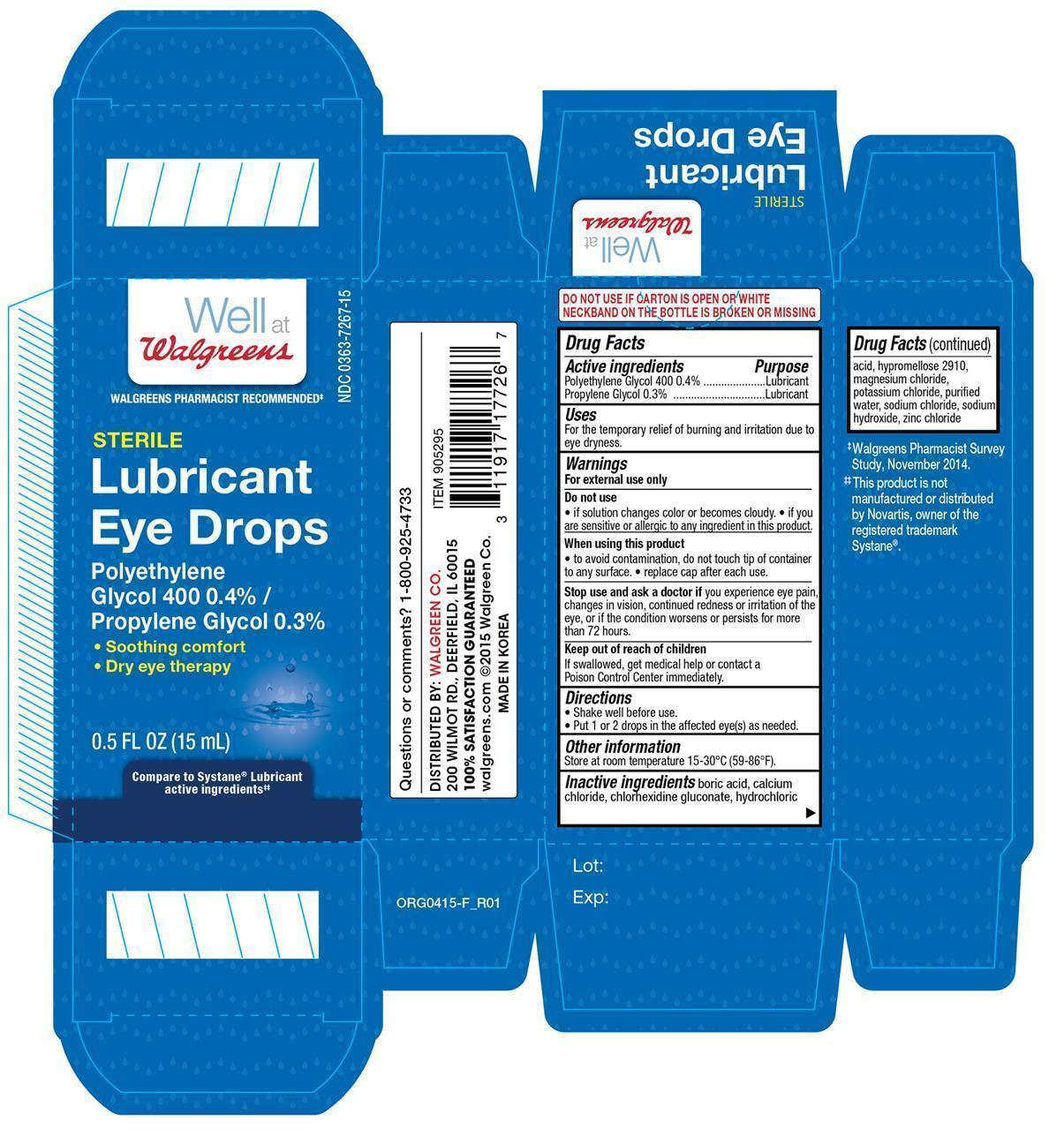 DRUG LABEL: Walgreens Lubricant Eye
NDC: 0363-7267 | Form: SOLUTION/ DROPS
Manufacturer: Walgreen Company
Category: otc | Type: HUMAN OTC DRUG LABEL
Date: 20150922

ACTIVE INGREDIENTS: POLYETHYLENE GLYCOL 400 4 mg/1 mL; PROPYLENE GLYCOL 3 mg/1 mL
INACTIVE INGREDIENTS: BORIC ACID; CALCIUM CHLORIDE; CHLORHEXIDINE GLUCONATE; HYDROCHLORIC ACID; MAGNESIUM CHLORIDE; POTASSIUM CHLORIDE; WATER; SODIUM CHLORIDE; SODIUM HYDROXIDE; ZINC CHLORIDE

Active ingredients Purpose

Polyethylene Glycol 400 0.4%....................................Lubricant

Propylene Glycol 0.3%..............................................Lubricant

Uses

For the temporary relief of burning and irritation due to eye dryness.

WARNINGS

For external use only

Do not use

- if solution changes color becomes cloudy.
- if you are sensitive or allergiv to any ingredient in this product.

When using this product

- to avoid contamination, do not touch tip of container to any surface.
- replace cap after each use.

Stop use and ask a doctor if you have experience eye pain, changes in vision, continued redness or irritation of the eye, or if the condition worsens or persists for more than 72 hours.

Keep out of reach of children

If swallowed, get medical help or contact a Poison Control Center immediately.

Directions

- Shake well before use.
- Put 1 or 2 drops in the affected eye(s) as needed.

Other information

Store at room temperature 15-30°C (59-86°F)

Inactive ingredients

boric acid, calcium chloride, chlorhexidine gluconate, hydrochloric acid, hypromellose 2910, magnesium chloride, potassium chloride, purified water, sodium chloride, sodium hydroxide, zinc chloride

DOSAGE AND ADMINISTRATION

Distributed by:

Walgreen Co.

200 Wilmot Rd.

Deerfield, IL 60015

Made in Korea